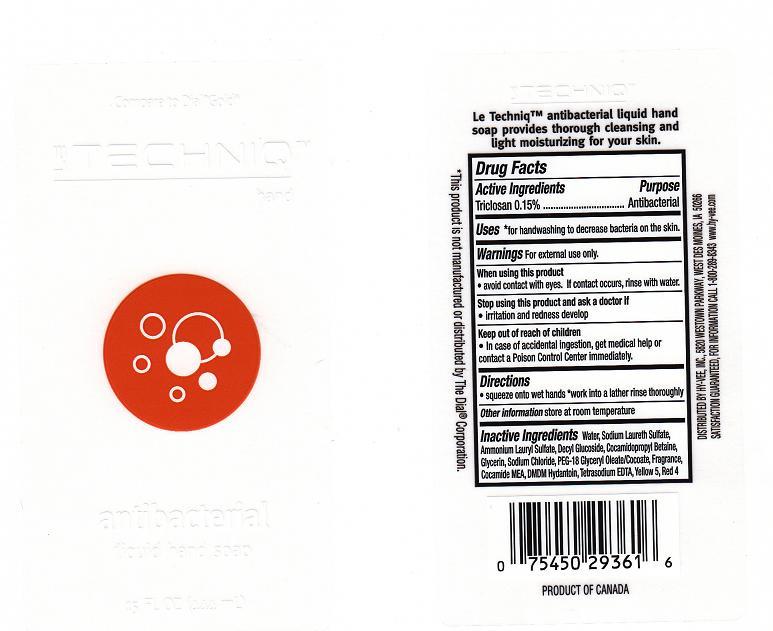 DRUG LABEL: ANTIBACTERIAL
NDC: 42507-220 | Form: LIQUID
Manufacturer: HYVEE INC
Category: otc | Type: HUMAN OTC DRUG LABEL
Date: 20110609

ACTIVE INGREDIENTS: TRICLOSAN 0.15 mL/100 mL
INACTIVE INGREDIENTS: WATER; AMMONIUM LAURYL SULFATE; SODIUM LAURETH SULFATE; DECYL GLUCOSIDE; GLYCERIN; SODIUM CHLORIDE; GLYCERYL MONOOLEATE; COCO MONOETHANOLAMIDE; DMDM HYDANTOIN; EDETATE SODIUM; FD&C YELLOW NO. 5; FD&C RED NO. 4; COCAMIDOPROPYL BETAINE

DRUG FACTS

ACTIVE INGREDIENT

TRICLOSAN 0.15%

PURPOSE

ANTIBACTERIAL

USES

FOR HANDWASHING TO DECREASE BACTERIA ON THE SKIN.

WARNINGS

FOR EXTERNAL USE ONLY.

WHEN USING THIS PRODUCT

AVOID CONTACT WITH EYES. IF CONTACT OCCURS, RINSE WITH WATER.

STOP USING THIS PRODUCT AND ASK A DOCTOR IF

IRRITATION AND REDNESS DEVELOP.

KEEP OUT OF REACH OF CHILDREN

IN CASE OF ACCIDENTAL INGESTION, GET MEDICAL HELP OR CONTACT A POISON CONTROL CENTER IMMEDIATELY.

DIRECTIONS

SQUEEZE ONTO WET HANDS. WORK INTO A LATHER RINSE THROUGHLY.

OTHER INFORMATION

STORE AT ROOM TEMPERATURE.

INACTIVE INGREDIENT

WATER, SODIUM LAURETH SULFATE, AMMONIUM LAURYL SULFATE, DECYL GLUCOSIDE, COCAMIDOPROPYL BETAINE, GLYCERIN, SODIUM CHLORIDE, PEG-18 GLYCERYL OLEATE/COCOATE, FRAGRANCE, COCAMIDE MEA, DMDM HYDANTOIN, TETRASODIUM EDTA, YELLOW 5 (CI 19140), RED 4 (CI 14700).